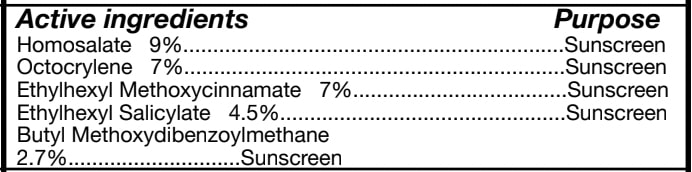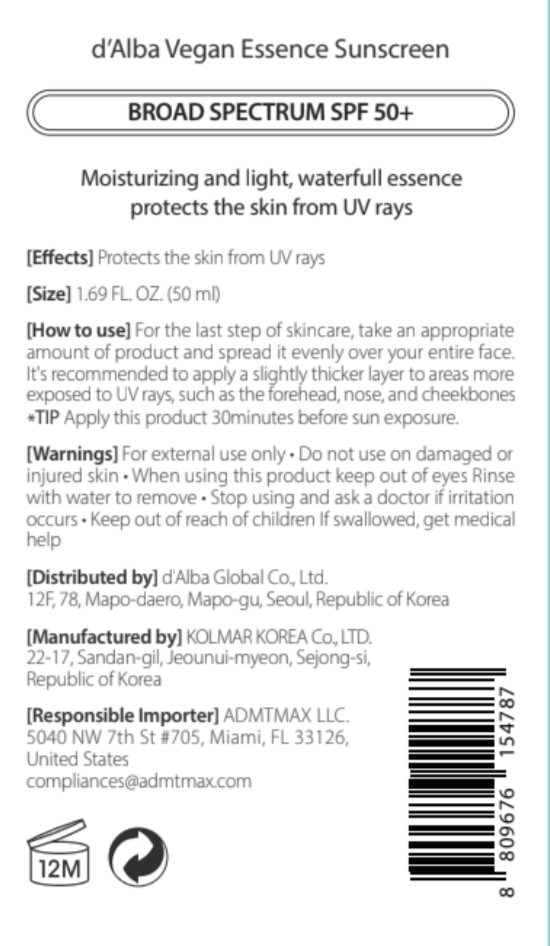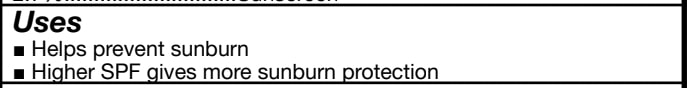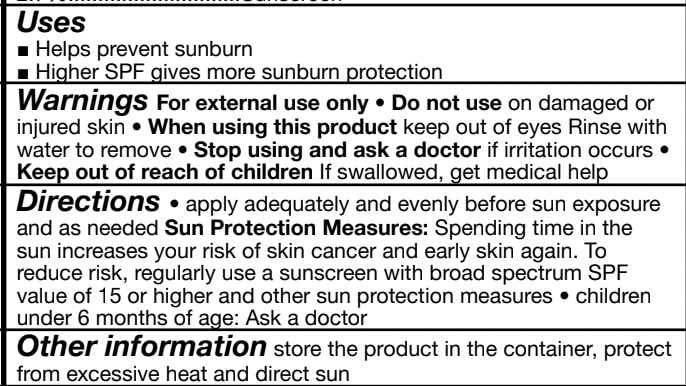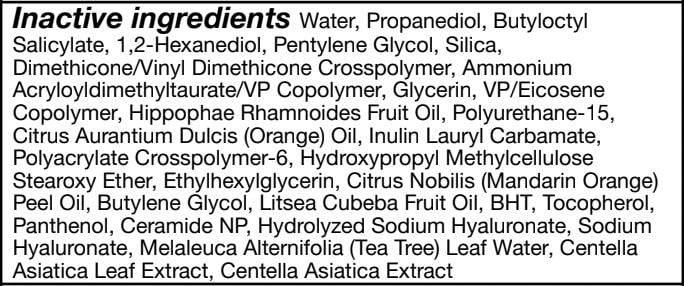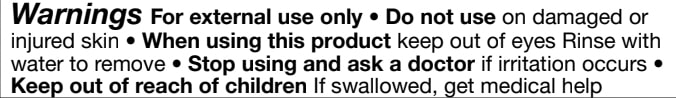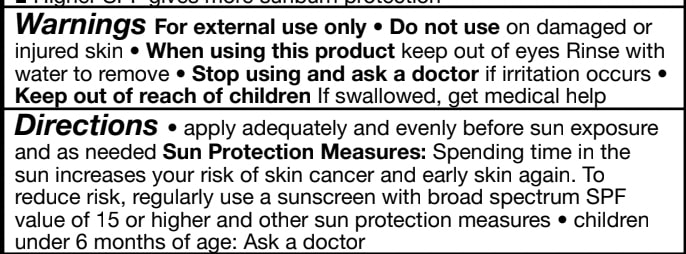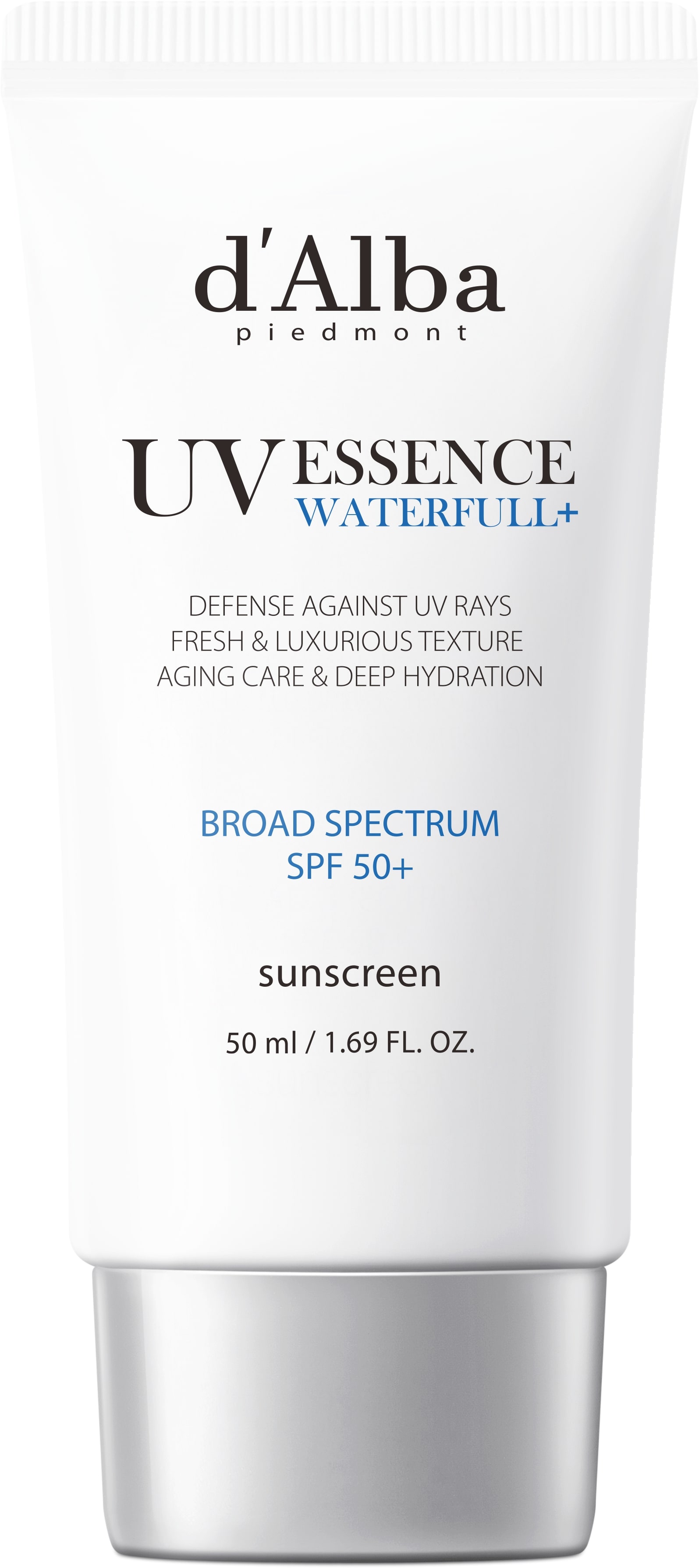 DRUG LABEL: dAlba Vegan Essence Sunscreen
NDC: 84662-020 | Form: CREAM
Manufacturer: ADMTMAX LLC
Category: otc | Type: HUMAN OTC DRUG LABEL
Date: 20250608

ACTIVE INGREDIENTS: HOMOSALATE 9 mg/50 mL
INACTIVE INGREDIENTS: 1,3-DIMETHYLBUTYL SALICYLATE

d'Alba Vegan Essence Sunscreen

General Precautions